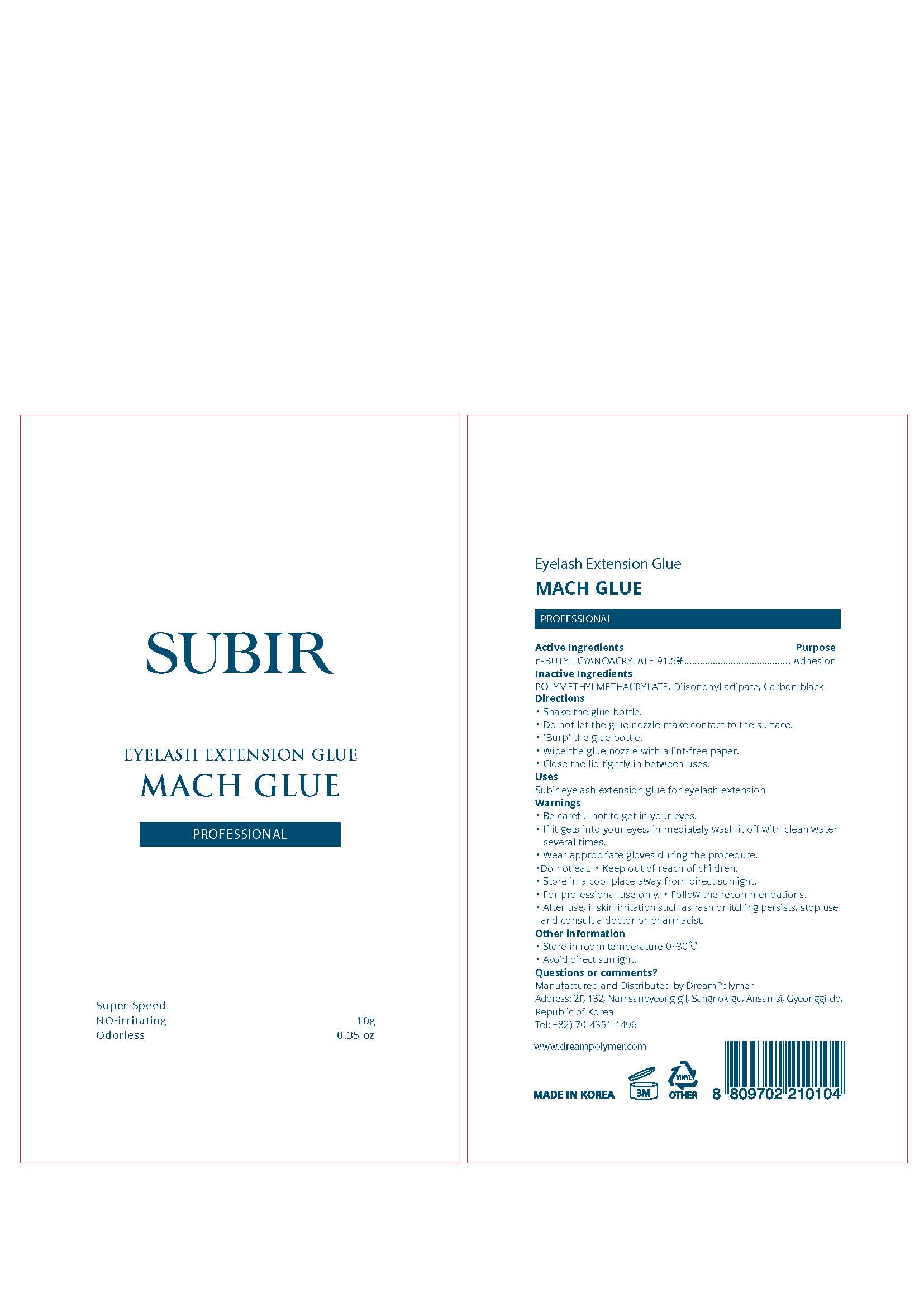 DRUG LABEL: SUBIR EYELASH
NDC: 81716-001 | Form: CREAM
Manufacturer: Dream Polymer
Category: otc | Type: HUMAN OTC DRUG LABEL
Date: 20210330

ACTIVE INGREDIENTS: 2-OCTYL CYANOACRYLATE 9.15 g/10 g
INACTIVE INGREDIENTS: Diisononyl adipate

Active Ingredient(s)

n-BUTYL CYANOACRYLATE 91.5%

Purpose

Purpose:Adhesion

Use

Subir eyelash extension glue for eyelash extension

Warnings

・ Be careful not to get in your eyes.
・ If it gets into your eyes, immediately wash it off with clean water
several times.
・ Wear appropriate gloves during the procedure.
・Do not eat. ・ Keep out of reach of children.
・ Store in a cool place away from direct sunlight.
・ For professional use only. ・ Follow the recommendations.
・ After use, if skin irritation such as rash or itching persists, stop use
and consult a doctor or pharmacist.

 Keep out of reach of children.

Directions

・ Shake the glue bottle.
・ Do not let the glue nozzle make contact to the surface.
・ 'Burp' the glue bottle.
・ Wipe the glue nozzle with a lint-free paper.
・ Close the lid tightly in between uses.

Other information

・ Store in room temperature 0~30℃
・ Avoid direct sunlight.

Inactive ingredients

POLYMETHYLMETHACRYLATE, Diisononyl adipate, Carbon black